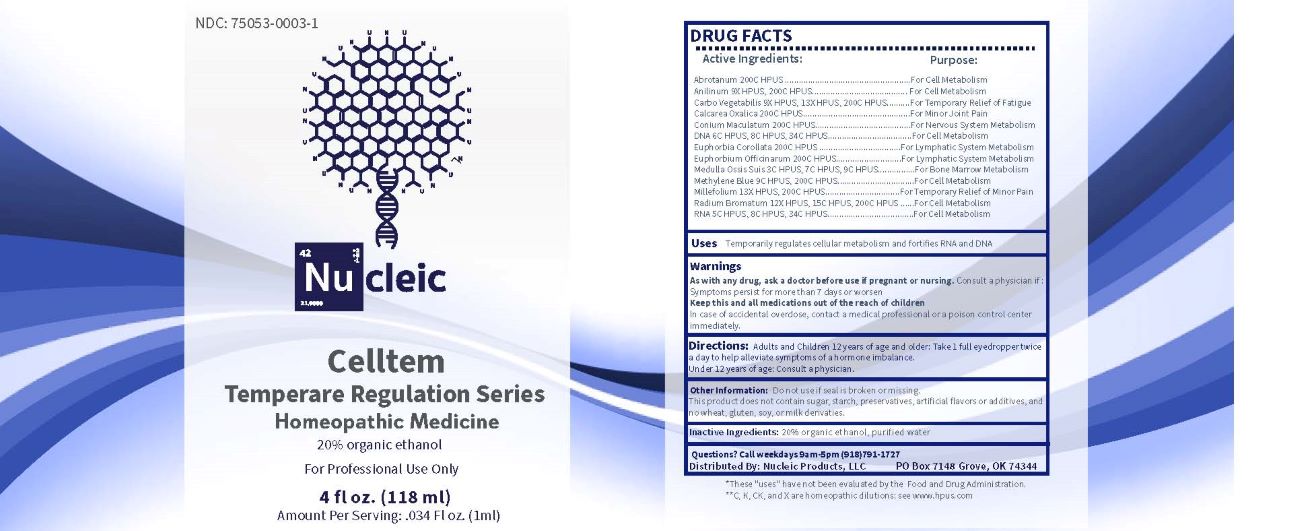 DRUG LABEL: Celltem
NDC: 75053-0003 | Form: LIQUID
Manufacturer: Nucleic Products, LLC
Category: homeopathic | Type: HUMAN OTC DRUG LABEL
Date: 20250320

ACTIVE INGREDIENTS: ACTIVATED CHARCOAL 9 [hp_X]/1 mL; ANILINE 9 [hp_X]/1 mL; RADIUM BROMIDE 12 [hp_X]/1 mL; ACHILLEA MILLEFOLIUM WHOLE 13 [hp_X]/1 mL; SUS SCROFA BONE MARROW 3 [hp_C]/1 mL; SACCHAROMYCES CEREVISIAE RNA 5 [hp_C]/1 mL; HERRING SPERM DNA 6 [hp_C]/1 mL; METHYLENE BLUE 9 [hp_C]/1 mL; ARTEMISIA ABROTANUM FLOWERING TOP 200 [hp_C]/1 mL; CALCIUM OXALATE MONOHYDRATE 200 [hp_C]/1 mL; CONIUM MACULATUM FLOWERING TOP 200 [hp_C]/1 mL; EUPHORBIA COROLLATA ROOT 200 [hp_C]/1 mL; EUPHORBIA RESINIFERA RESIN 200 [hp_C]/1 mL
INACTIVE INGREDIENTS: WATER; ALCOHOL

DRUG FACTS:

ACTIVE INGREDIENTS:

Abrotanum 200C HPUS, Anilinum 9X HPUS, 200C HPUS, Carbo Vegetabilis 9X HPUS, 13X HPUS, 200C HPUS , Calcarea Oxalica 200C HPUS, Conium Maculatum 200C HPUS, DNA 6C HPUS, 8C HPUS, 34C HPUS, Euphorbia Corollata 200C HPUS, Euphorbium Officinarum 200C HPUS, Medulla Ossis Suis 3C HPUS, 7C HPUS, 9C HPUS, Methylene Blue 9C HPUS, 200C HPUS, Millefolium 13X HPUS, 200C HPUS, Radium Bromatum 12X HPUS, 15C HPUS, 200C HPUS, RNA 5C HPUS, 8C HPUS, 34C HPUS.

PURPOSE:

Abrotanum - For Cell Metabolism, Anilinum – For Cell Metabolism, Carbo Vegetabilis – For Temporary Relief of Fatigue, Calcarea Oxalica – For Minor Joint Pain, Conium Maculatum – For Nervous System Metabolism, DNA – For Cell Metabolism, Euphorbia Corollata – For Lymphatic System Metabolism, Euphorbium Officinarum – For Lymphatic system Metabolism, Medulla Ossis Suis – For Bone Marrow Metabolism, Methylene Blue – For Cell Metabolism, Millefolium – For Temporary Relief of Minor Pain, Radium Bromatum – For Cell Metabolism, RNA – For Cell Metabolism

USES:

Temporarily regulates cellular metabolism and fortifies RNA and DNA.*

*These "uses" have not been evaluated by the Food and Drug Administration.

WARNINGS:

As with any drug, ask a doctor before use if pregnant or nursing. Consult a physician if: Symptoms persist for more than 7 days or worsen.

Keep this and all medications out of reach of children

In case of accidental overdose, contact a medical professional or a poison control center immediately.

Do not use if seal is broken or missing.

This Product does not contain sugar, starch, preservatives, artificial flavors or additives, and no wheat, gluten, soy, or milk derivatives.

KEEP OUT OF REACH OF CHILDREN:

In case of accidental overdose, contact a medical professional or a poison control center immediately.

DIRECTIONS:

Adults and Children 12 years of age and older: Take 1 full eyedopper twice a day to help alleviate symptoms of a hormone imbalance.

Under 12 years of age: Consult a physician.

INACTIVE INGREDIENTS:

20% organic ethanol, purified water

QUESTIONS:

Distributed By:
Nucleic Products, LLC

PO Box 7148 Grove, OK 74344

(918) 791-1727

PACKAGE LABEL DISPLAY:

NDC: 75053-0003-1

Nu cleic

Celltem

Homeopathic Medicine

For Professional Use Only

4 fl oz. (118 ml)